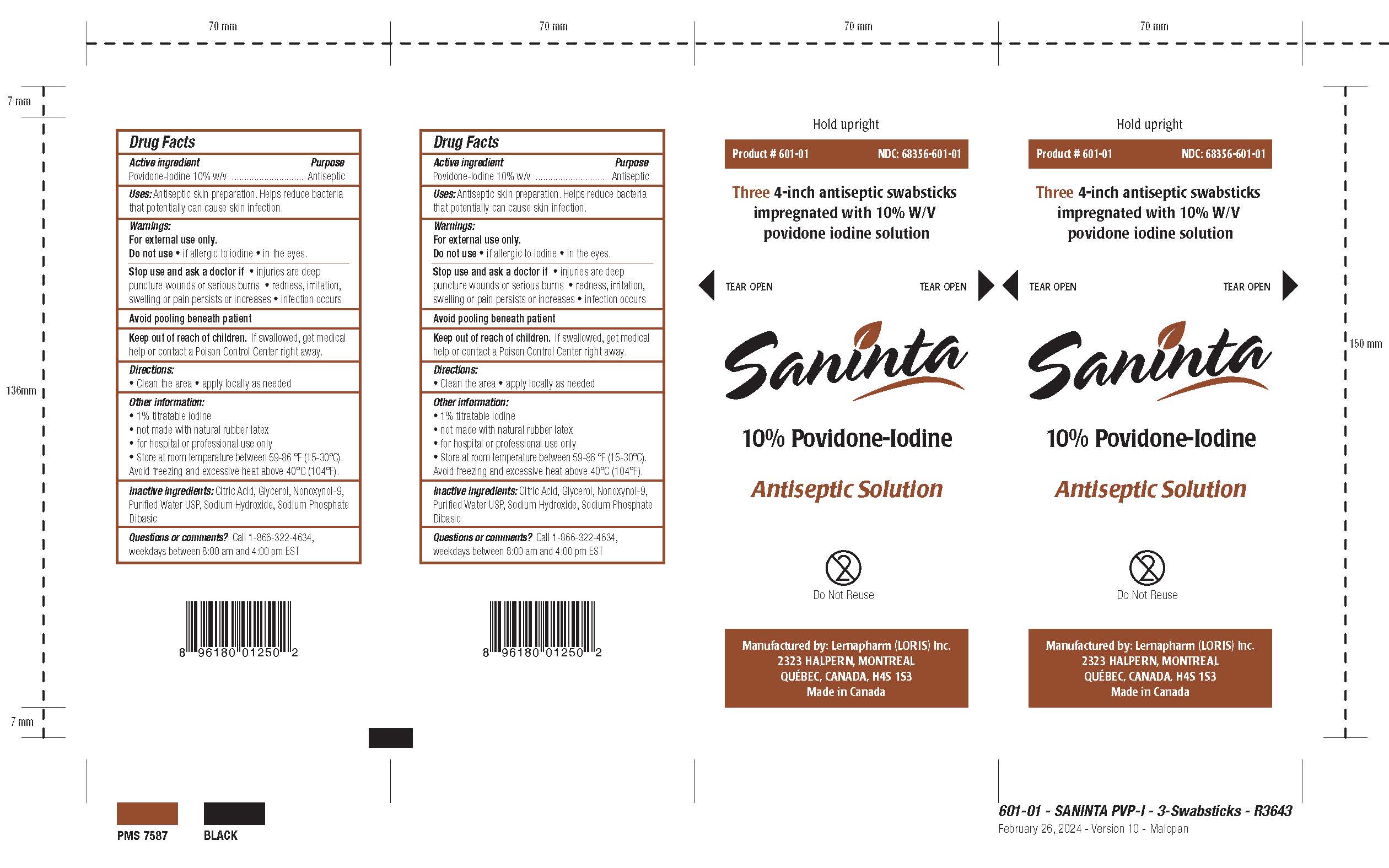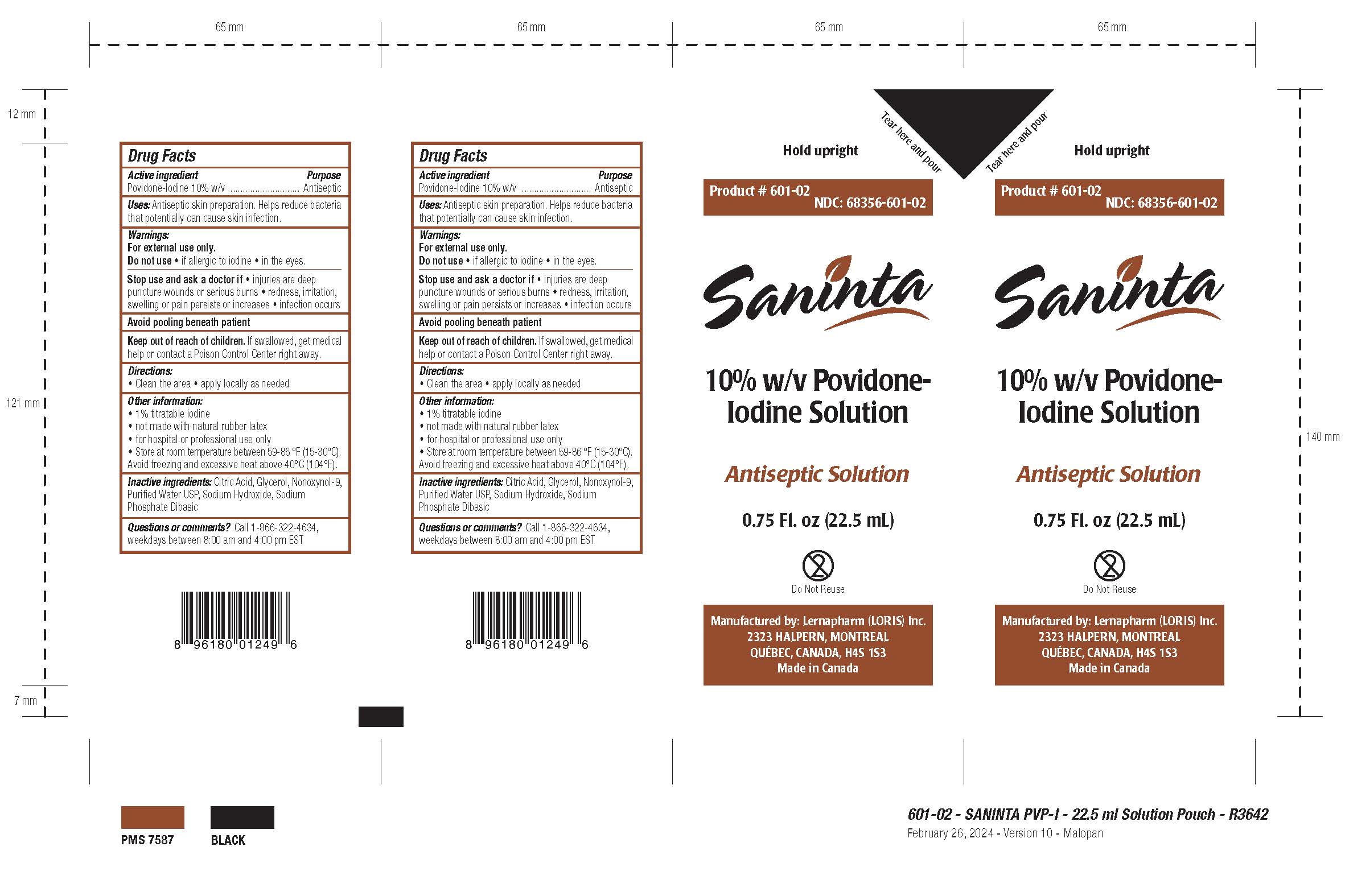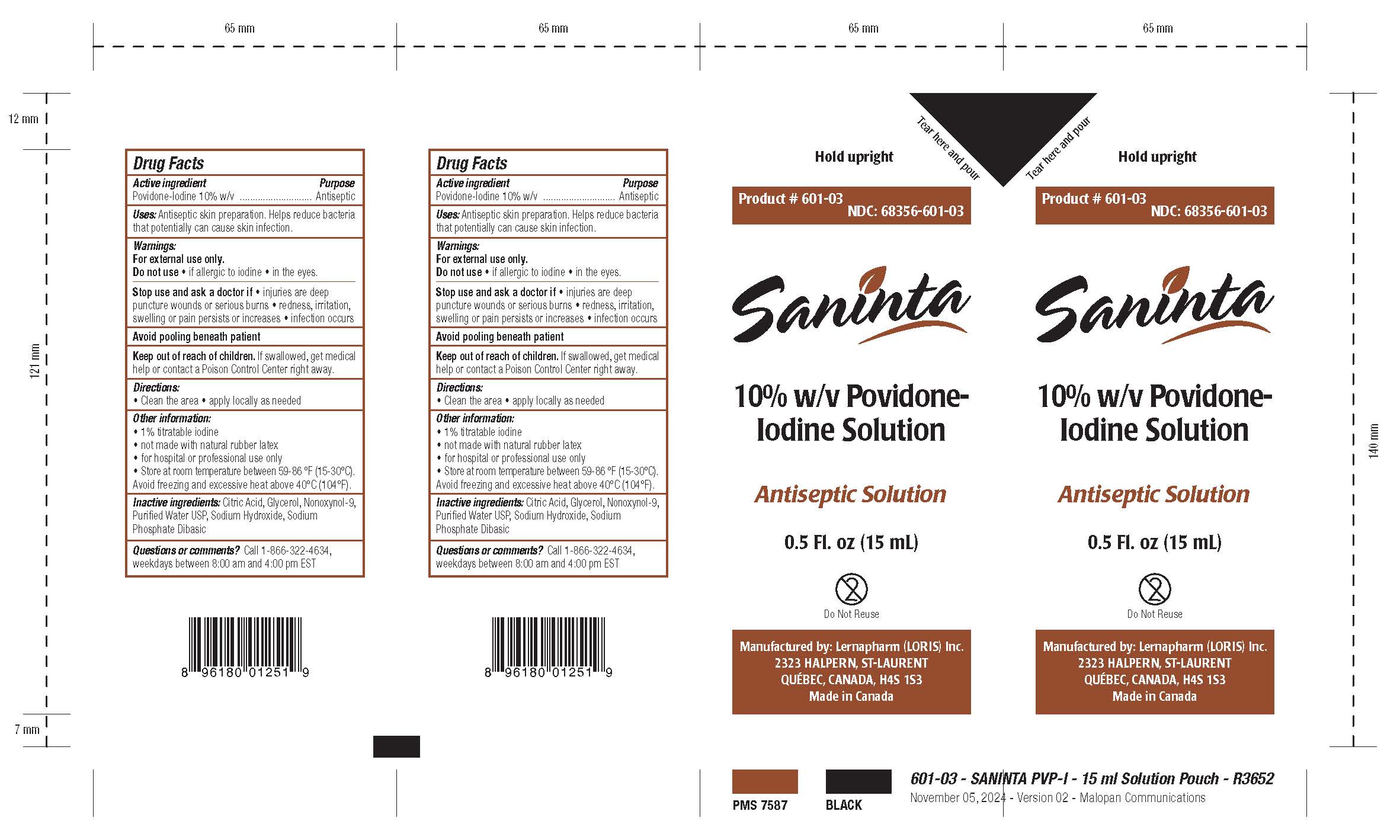 DRUG LABEL: Saninta 10% Povidone-Iodine
NDC: 68356-601 | Form: LIQUID
Manufacturer: Lernapharm
Category: otc | Type: HUMAN OTC DRUG LABEL
Date: 20241115

ACTIVE INGREDIENTS: POVIDONE-IODINE 100 mg/1 mL
INACTIVE INGREDIENTS: WATER; GLYCERIN; NONOXYNOL-9; SODIUM HYDROXIDE; SODIUM PHOSPHATE DIBASIC DIHYDRATE; ANHYDROUS CITRIC ACID

Drug Facts - Saninta 10% w/v Povidone-Iodine Solution

Active Ingredient

Povidone-Iodine 10% w/v

Purpose

Antiseptic

Use

Antiseptic skin preparation. Helps reduce bacteria that potentially can cause skin infection.

Warnings

For external use only.

Do not use

- if allergic to iodine
- in the eyes

Stop use and ask a doctor

Stop use and ask a doctorif

- injuries are deep puncture wounds or serious burns
- redness, irritation, swelling or pain persists or increases
- infection occurs

Avoid pooling beneath patient

Keep out of reach of children. If swallowed, get medical help or contact a Poison Control Center right away.

Directions

- Clean the area.
- apply locally as needed

Other Information

- 1% titratable iodine
- not made with natural rubber latex
- for hospital or professional use only
- Store at room temperature between 59-86ºF (15 - 30ºC).
- Avoid freezing and excessive heat above 40ºC (104ºF).

Inactive ingredients

Citric Acid, Glycerol, Nonoxynol-9, Purified Water USP, Sodium Hydroxide, Sodium Phosphate Dibasic

Questions or Comments? Tel.: 1-866-322-4634, weekdays between 8:00 am and 4:00 pm EST

Package Label - Principal Display Panel

NDC: 68356-601-01 / 68356-601-601-02 / 68356-601-03

Product # 601-01 / 601-02 / 601-03

Hold upright

[Tear here and pour]

[Three 4-inch antiseptic swabsticks impregnated with 10% W/V povidone-iodine solution]

[Tear open]

Saninta

Antiseptic Solution

10% w/v Povidone-Iodine Solution

10% Povidone-Iodine

[0.75 Fl. oz (22.5 mL)]

[0.5 Fl. oz (15 mL)]

Do Not Reuse

multiple-use cross-through logo

UPC Code

Manufactured by:

Lernapharm (LORIS) Inc.

2323 HALPERN, MONTREAL

QUEBEC, CANADA H4S 1S3

Made in Canada

LOT #: XXXX

EXP.: MM/YYYY